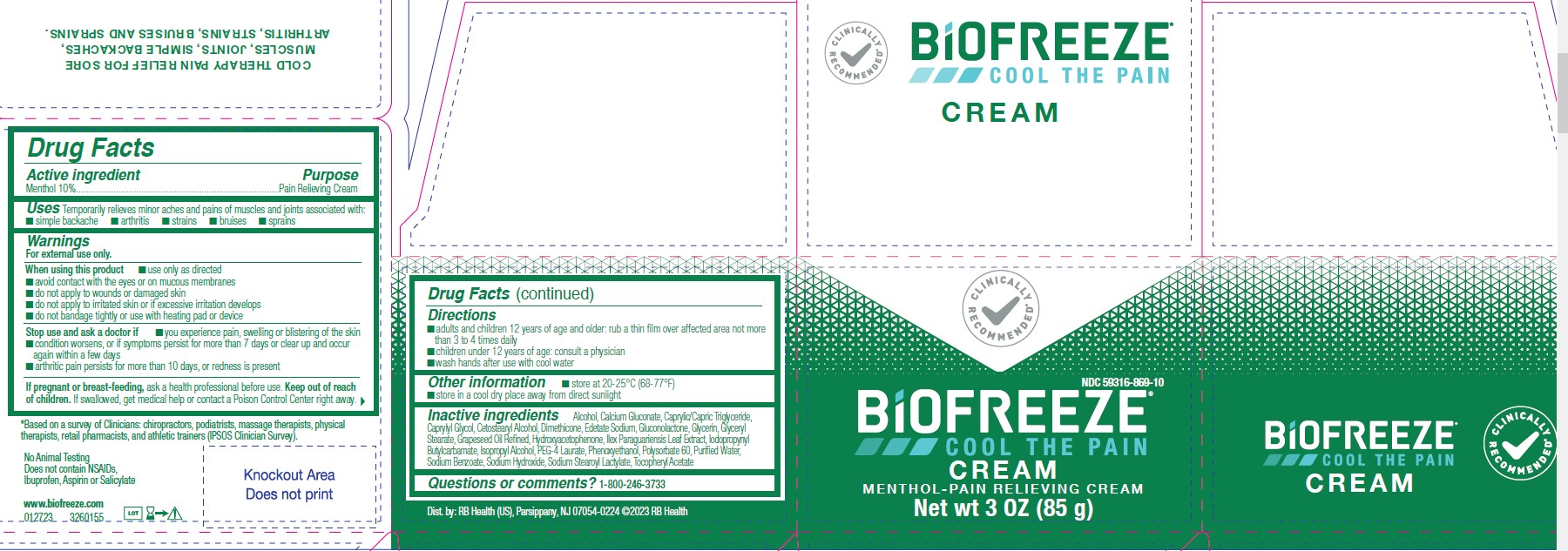 DRUG LABEL: Biofreeze
NDC: 59316-869 | Form: CREAM
Manufacturer: RB Health (US) LLC
Category: otc | Type: HUMAN OTC DRUG LABEL
Date: 20240110

ACTIVE INGREDIENTS: MENTHOL, UNSPECIFIED FORM 100 mg/1 g
INACTIVE INGREDIENTS: ALCOHOL; CETOSTEARYL ALCOHOL; ISOPROPYL ALCOHOL; PEG-4 LAURATE; GLYCERIN; CALCIUM GLUCONATE; MEDIUM-CHAIN TRIGLYCERIDES; CAPRYLYL GLYCOL; DIMETHICONE; GLUCONOLACTONE; GLYCERYL MONOSTEARATE; HYDROXYACETOPHENONE; ILEX PARAGUARIENSIS LEAF; IODOPROPYNYL BUTYLCARBAMATE; PHENOXYETHANOL; POLYSORBATE 60; SODIUM BENZOATE; SODIUM HYDROXIDE; SODIUM STEAROYL LACTYLATE; EDETATE SODIUM; .ALPHA.-TOCOPHEROL ACETATE; GRAPE SEED OIL; WATER

Biofreeze Cream

Active Ingredients:

Menthol USP 10%

Purpose

Cooling Pain Relief

Uses:

Temporary relief from minor aches and pains of sore muscles and joints associated with: • arthritis • backache • strains • sprains

Warnings:

For external use only

Ask a doctor before use if you have:

Sensitive skin

When using this product:

• Avoid contact with the eyes or mucous membranes • Do not apply to wounds or damaged skin • Do not use with other ointments, creams, sprays or liniments • Do not apply to irritated skin or if excessive irritation develops • Do not bandage • Wash hands after use with cool water • Do not use with heating pad or device • Store in a cool dry place

Stop use and ask a doctor if:

Condition worsens, or if symptoms persist for more than 7 days, or clear up and recur

If pregnant or breastfeeding:

Ask a health professional before use

Keep out of reach of children:

If accidentally ingested, get medical help or contact a Poison Control Center immediately

Directions:

• Adults and Children 12 years of age and older:Rub a thin film over affected areas not more four times daily; massage not necessary
• Children under 12 years of age:Consult physician

Inactive Ingredients:

Caprylic/Capric Triglyceride, Caprylyl Glycol, Alcohol, Dimethicone, Gluconolactone Glycerin, Glyceryl Stearate, Hydroxyacetophenone, Ilex Paraguariensis Leaf Extract, Iodopropynyl Butylcarbamate, Phenoxyethanol, Polysorbate 60, Sodium Benzoate, Sodium Hydroxide, Sodium Stearoyl Lactylate, Tocopheryl Acetate, Vitis Vinifera (Grape) Seed Oil, Water,Calcium Gluconate, Cetostearyl Alcohol, Edetate Sodium, Isopropyl Alcohol, PEG-4 Laurate

Questions or Comments:

1-800-246-3733